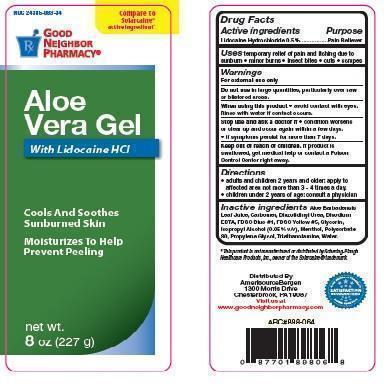 DRUG LABEL: Good Neighbor Pharmacy Aloe Vera
NDC: 24385-083 | Form: GEL
Manufacturer: Amerisourcebergen Drug Corporation
Category: otc | Type: HUMAN OTC DRUG LABEL
Date: 20150722

ACTIVE INGREDIENTS: LIDOCAINE HYDROCHLORIDE 500 g/100000 mg
INACTIVE INGREDIENTS: ALOE VERA LEAF; CARBOMER 940; DIAZOLIDINYL UREA; EDETATE DISODIUM; FD&C BLUE NO. 1; FD&C YELLOW NO. 5; GLYCERIN; ISOPROPYL ALCOHOL; MENTHOL; POLYSORBATE 80; PROPYLENE GLYCOL; TROLAMINE; WATER

Good Neighbor Pharmacy Aloe Vera

Drug Facts

Active Ingredients

Lidocaine Hydrochloride 0.5%

PURPOSE

Pain Reliever

For external use only

Do not use in large quantities, particularly over raw or blistered areas.

When using this product

• avoid contact with eyes.

Rinse with water if contact occurs.

Stop use and ask a doctor if

• condition worsens

or clear up and occur again within a few days.

• if symptoms persist for more than 7 days.

Keep out of reach of children.

If product is swallowed, get medical help or contact a Poison Control Center right away.

DOSAGE AND ADMINISTRATION

• adults and children 2 years and older: apply to affected area not more than 3 - 4 times a day. • children under 2 years of age: consult a physician

INACTIVE INGREDIENT

Aloe Barbadensis Leaf Juice, Carbomer, Diazolidinyl Urea, Disodium EDTA, FD&C Blue #1, FD&C Yellow #5, Glycerin, Isopropyl Alcohol (0.05% v/v), Menthol, Polysorbate 80, Propylene Glycol, Triethanolamine, Water.

This product is not manufactured or distributed by Schering-Plough

Healthcare Products, Inc., owner of the Solarcaine® trademark.

Distributed By

AmerisourceBergen

1300 Morris Drive

Chesterbrook, PA 19087

Visit us at

www.goodneighborpharmacy.com